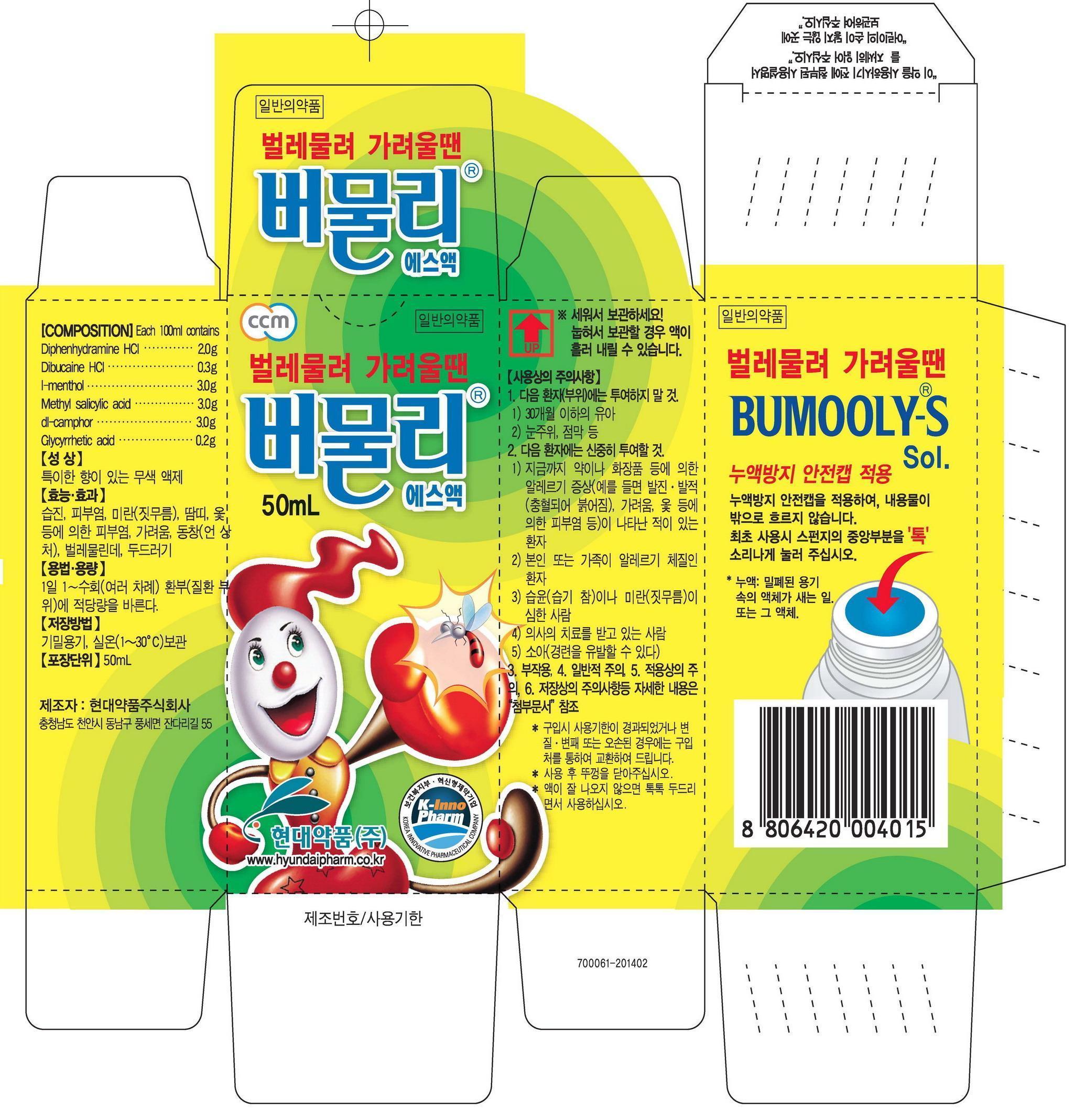 DRUG LABEL: Bumooly-S
NDC: 68994-4001 | Form: SOLUTION
Manufacturer: Scott Holdings Co., Ltd.
Category: otc | Type: HUMAN OTC DRUG LABEL
Date: 20140516

ACTIVE INGREDIENTS: METHYL SALICYLATE 3 g/100 mL
INACTIVE INGREDIENTS: MENTHOL; CAMPHOR (SYNTHETIC); DIPHENHYDRAMINE HYDROCHLORIDE; DIBUCAINE HYDROCHLORIDE

Drug Facts

ACTIVE INGREDIENT

methyl salicylate

INACTIVE INGREDIENT

camphor, menthol, glycyrrhetic acid, diphenhydramine hcl, dibucaine hcl

PURPOSE

aczema, dermatitis, erosion, miliaria, pruritus, pernio, insect bite, hives

keep out or reach of the children

INDICATIONS AND USAGE

apply to the affected area once to several times a day

WARNINGS

avoid contact with eyes, if this product splashes in to your eyes, wash immediately with water

DOSAGE AND ADMINISTRATION

for external use only